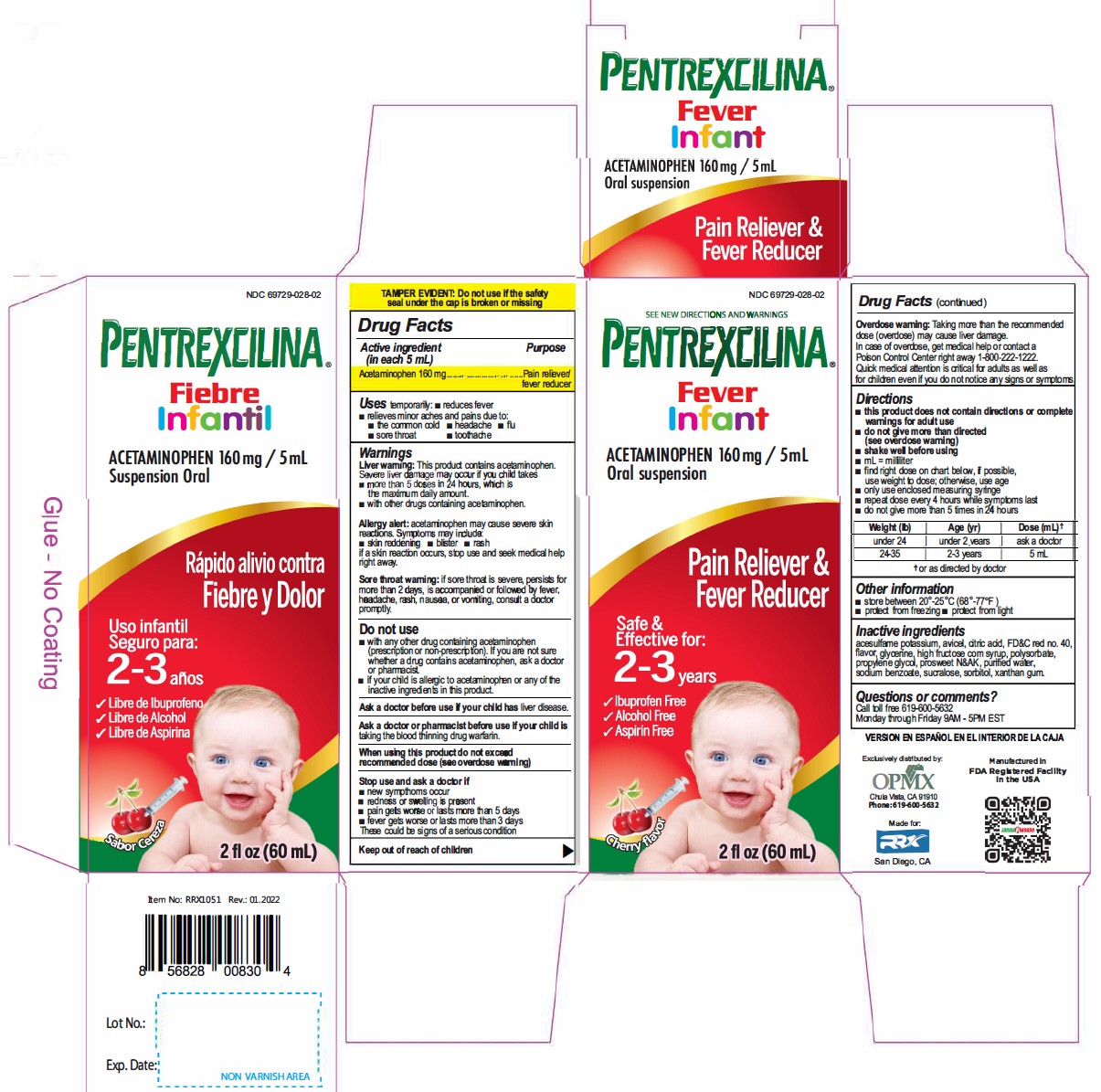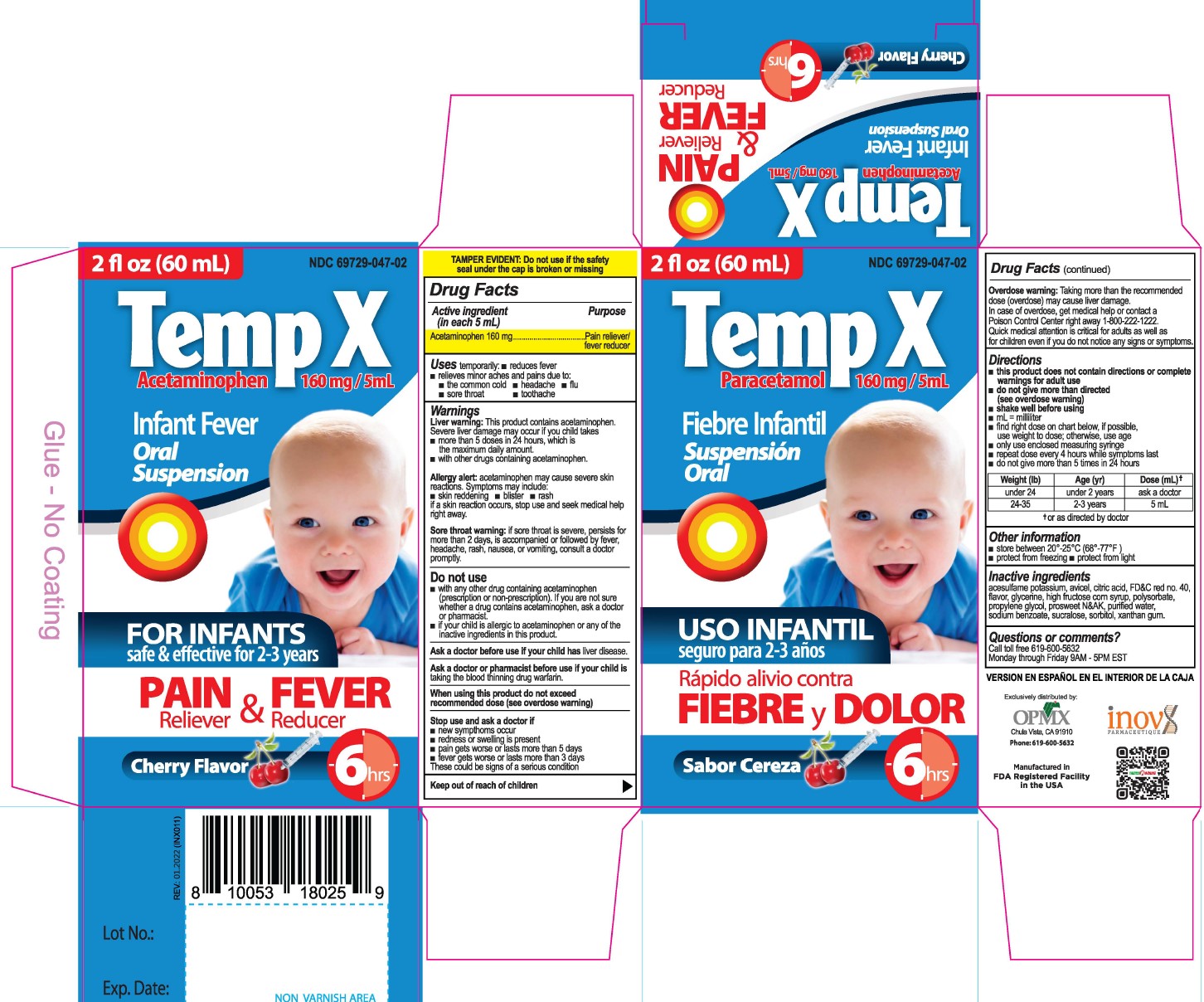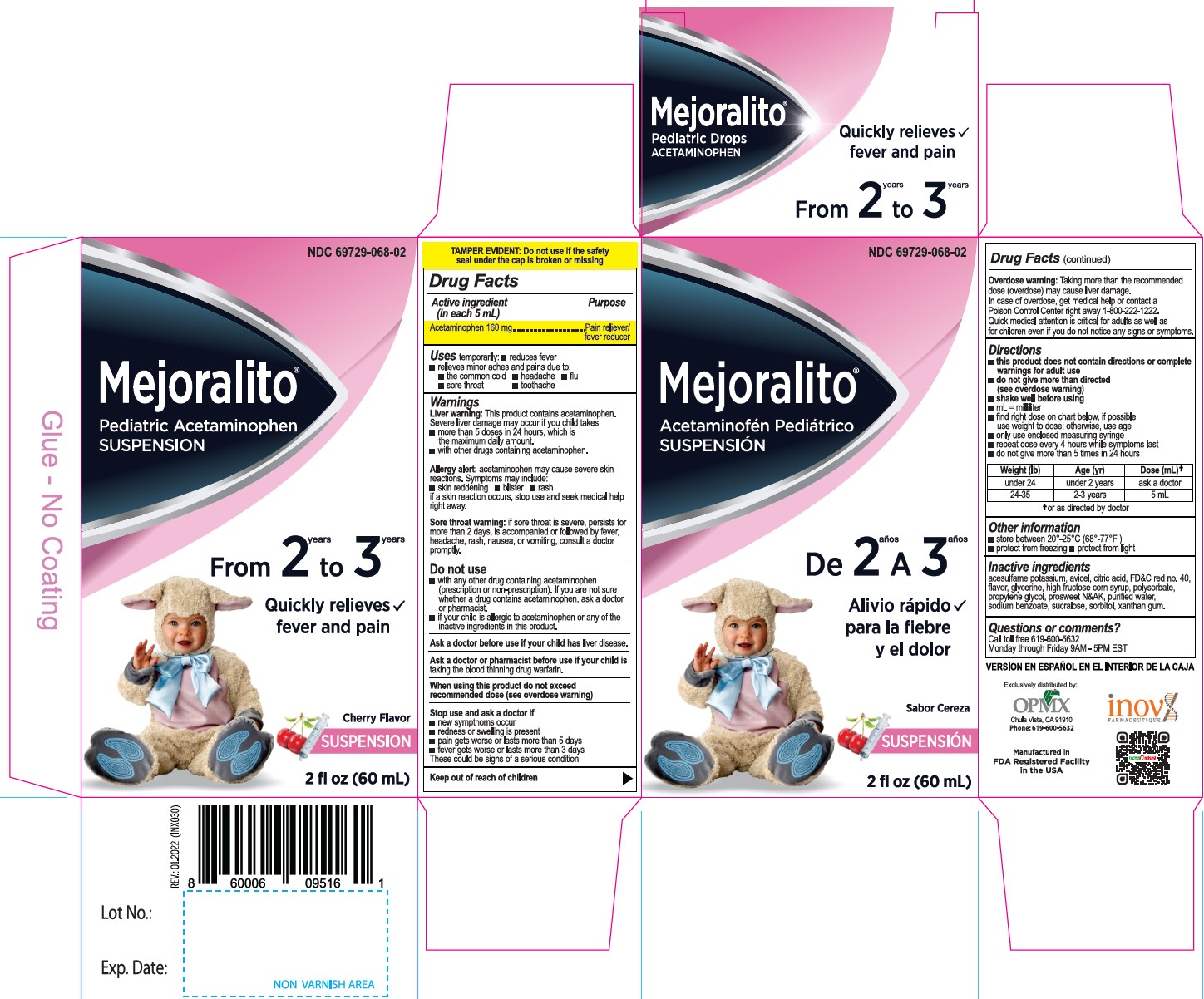 DRUG LABEL: Acetaminophen
NDC: 69729-028 | Form: SUSPENSION
Manufacturer: OPMX LLC
Category: otc | Type: HUMAN OTC DRUG LABEL
Date: 20250829

ACTIVE INGREDIENTS: ACETAMINOPHEN 160 mg/5 mL
INACTIVE INGREDIENTS: ACESULFAME POTASSIUM; MICROCRYSTALLINE CELLULOSE; ANHYDROUS CITRIC ACID; FD&C RED NO. 40; GLYCERIN; HIGH FRUCTOSE CORN SYRUP; POLYSORBATE 20; PROPYLENE GLYCOL; WATER; SODIUM BENZOATE; SUCRALOSE; SORBITOL; XANTHAN GUM

Active Ingredient(in each 5mL) Purpose

Acetaminophen 160 mg............. Pain reliever/fever reducer

PURPOSE

Pain Reliever & Fever Reducer

Uses

temporarily:

- reduces fever
- relieves minor aches and pains due to:
- the common cold
- headache
- flu
- sore throat
- toothache

Warnings

Liver warning: This product contains acetaminophen.
Severe liver damage may occur if your child takes takes

- more than 5 doses in 24 hours. which is the maximum daily amount.
- with other drugs containing acetaminophen.

Allergy alert: acetaminophen may cause severe skin reactions. Symptoms may include:

- skin reddening
- blister
- rash

if a skin reaction occurs, stop use and seek medical help right away.

Sore throat warning: if sore throat is severe, persists for more than 2 days, is accompanied or followed by fever, headache, rash, nausea, or vomiting, consult a doctor promptly.

Do not use

- with any other drug containing acetaminophen (prescnption or non-prescription). If you are not sure whether a drug contains acetaminophen, ask a doctor or pharmacist.
- if your child is allergic to acetaminophen or any of the inactive ingredients in this product.

Ask a doctor before use if your child has liver disease.

Ask a doctor or pharmacist before use if your child is taking the blood thinning drug warfarin.

When using this product do not exceed recommened dose (see overdose warning)

Stop use and ask a doctor if

- new sympthoms occur
- redness or swelling is present
- pain gets worse or lasts more than 5 days
- fever gets worse or lasts more than 3 days

These could be signs of a serious condition

Keep out of reach of children.

OVERDOSAGE

Overdose warning: Taking more than the recommended dose (overdose) may cause liver damage. In case of overdose, get medical help or contact a Poison Control Center right away 1-800-222-1222. Quick medical attention is critical for adults as well as for children even if you do not notice any signs or symptoms.

Directions

- this product does not contain directions or complete warnings for adult use
- do not give more than directed (see overdose warning)
- shake well before using
- mL= millilitar
- find right dose on chart below, if possible, use weight to dose; otherwise, use age
- only use enclosed measuring syringe
- repeat dose every 4 hours while symptoms last
- do not give more than 5 times in 24 hours

Weight (Ib) | Age (yr) | Dose (mL) [or as directed by doctor]
under 24 | under 2 years | ask a doctor
24-35 | 2-3 years | 5 mL

Other information

- store between 20°-25°C (68°-77°F)
- protect from freezing
- protect from light

Questions or comments?
Call toll free 619-600-5632
Monday through Fnday 9AM - 5PM EST

Inactive ingredients

acesulfame potassium, avicel, citric acid, FD&C red no. 40, flavor, glycerine, high fructose corn syrup, polysorbate, propylene glycol, prosweet N&AK, purified water, sodium benzoate, sucralose, sorbitol, xanthan gum.

Distributed by:
OPMX, Chula Vista CA 91910